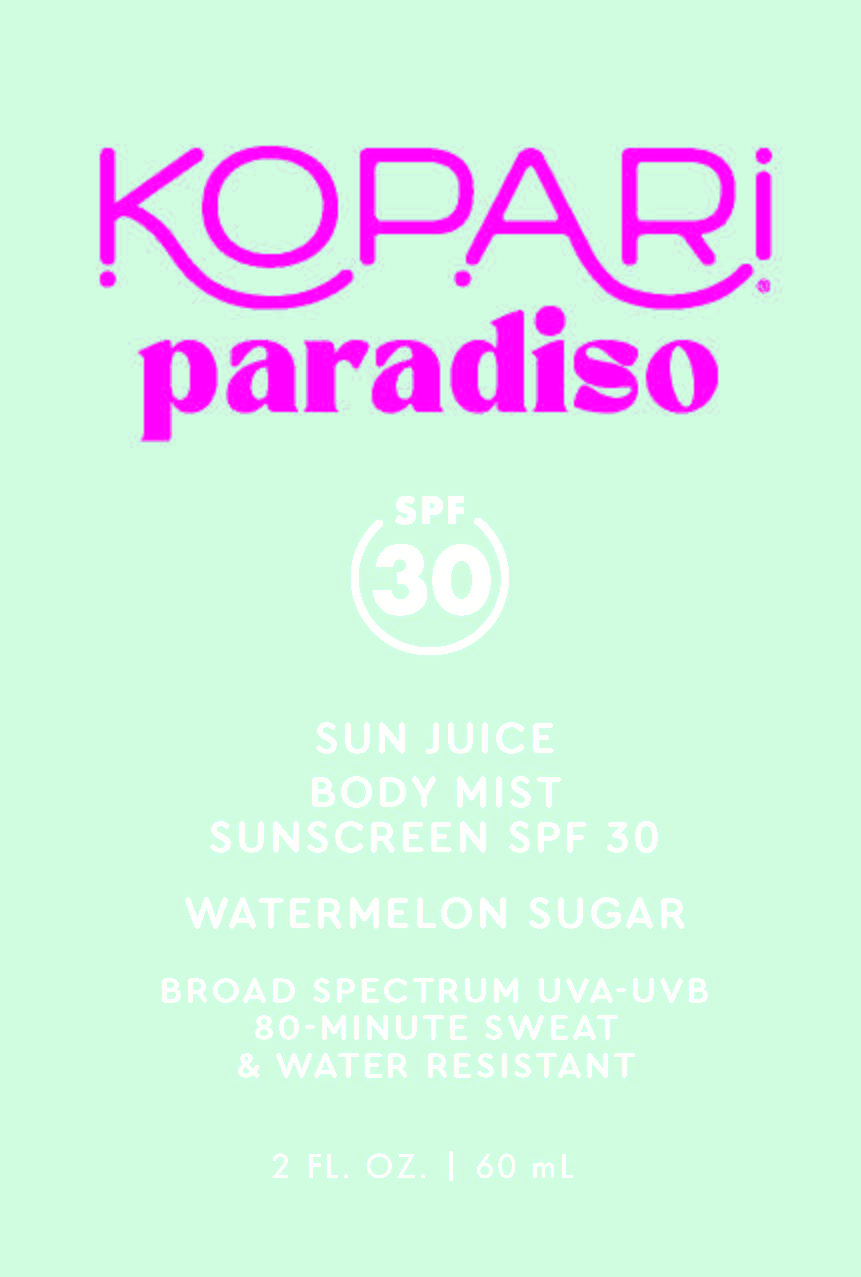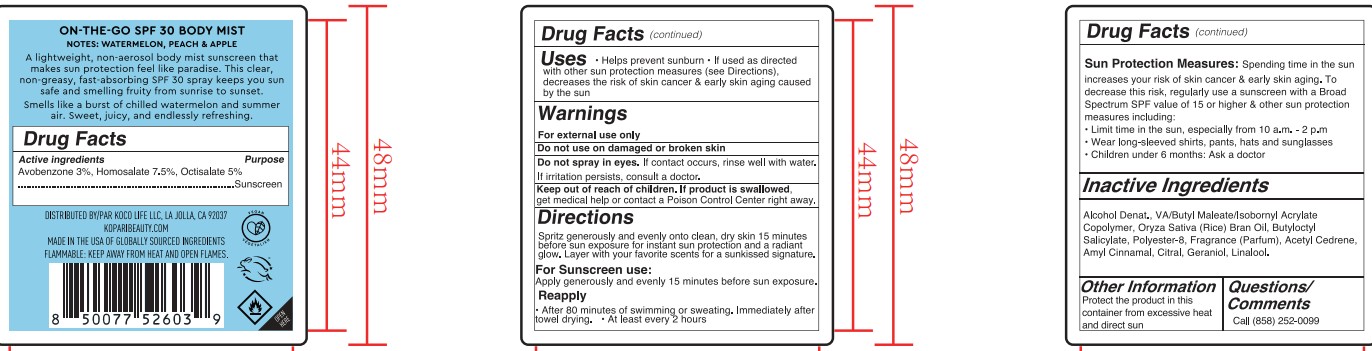 DRUG LABEL: Sun Juice Body Mist Sunscreen SPF30 - Watermelon Sugar PARADISO
NDC: 84130-020 | Form: SPRAY
Manufacturer: Koco Life LLC
Category: otc | Type: HUMAN OTC DRUG LABEL
Date: 20250910

ACTIVE INGREDIENTS: HOMOSALATE 75 mg/1 mL; OCTISALATE 50 mg/1 mL; AVOBENZONE 30 mg/1 mL
INACTIVE INGREDIENTS: ALCOHOL; VINYL ACETATE; DIBUTYL MALEATE; POLYESTER-8 (1400 MW, CYANODIPHENYLPROPENOYL CAPPED); ACETYL CEDRENE; ISOBORNYL ACRYLATE; ORYZA SATIVA (RICE) BRAN; GERANIOL; CITRAL; AMYL CINNAMAL; BUTYLOCTYL SALICYLATE; LINALOOL

Sun Juice Body Mist Sunscreen SPF30 - Watermelon Sugar PARADISO

Active ingredients

Avobenzone 3%, Homosalate 7.5%, Octisalate 5%

Purpose

Avobenzone 3%, Homosalate 7.5%, Octisalate 5%.........................Sunscreen

Uses

- Helps prevent sunburn
- If used as directed with other sun protection measures (see Directions), decreass the risk of skin cancer & early skin aging caused by the sun

Warnings

For external use only

Do not use on damaged or broken skin

WHEN USING

Do not spray in eyes. If contact occurs, rinse well with water. If irritation persists, consult a doctor.

Keep out of reach of children. If produt is swallowed, get medical help or contact a Poison Conrol Center right away.

Directions

Spritz generously and evenly onto clean, dry skin 15 minutes before sun exposure for instant sun protection and a radiant glow. Layer with your favorite scents for a sunkissed signature.

For Sunscreen use:

Apply generously and evenly 15 minutes before sun exposure.

Reapply

- After 80 minutes of swimming or sweating. Immediately after towel drying.
- At least every 2 hours

Sun Protection Mesures: Spending time in the sun increases your risk of skin cancer & early skin aging. To decrease this risk, regularly use a sunscreen with a Broad Spectrum SPF value of 15 or higher & other sun protection measures including:

- Limit time in the sun, especially from 10 a.m. - 2 p.m.
- Wear long-sleeved shirts, pants, hats and sunglasses
- Children under 6 months: Ask a doctor

Inactive ingredients

Alcohol Denat., VA/Butyl Maleate/Isobornyl Acrylate Copolymer, Oryza Sativa (Rice) Bran Oil, Butyloctyl Salicylate, Polyester-8, Fragrance (Parfum), Acetyl Cedrene, Amyl Cinnamal, Citral, Geraniol, Linalool.

Other information

Protect the product in this container from excessive heat and direct sun

Questions/Comments

Call (858) 252-0099

PACKAGE LABEL

Kopari

Paradiso

SPF 30

Sun Juice

Body Mist

Sunscreen SPF 30

Watermelon Sugar

Broad Spectrum UVA-UVB

80-Minute Sweat & Water Resistant

2 Fl Oz. | 60 mL